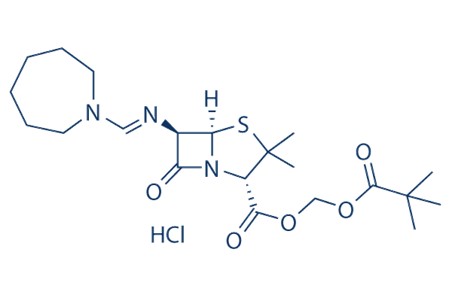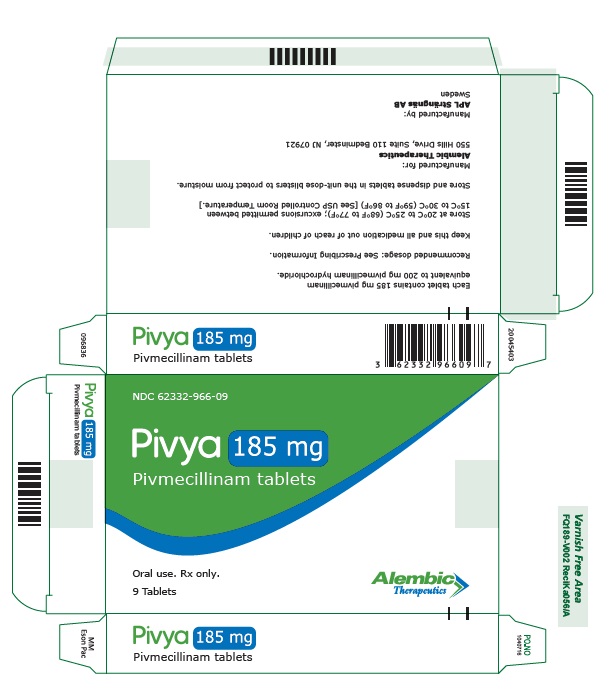 DRUG LABEL: PIVYA
NDC: 62332-966 | Form: TABLET, COATED
Manufacturer: Alembic Pharmaceuticals Inc.
Category: prescription | Type: HUMAN PRESCRIPTION DRUG LABEL
Date: 20251010

ACTIVE INGREDIENTS: PIVMECILLINAM HYDROCHLORIDE 185 mg/1 1
INACTIVE INGREDIENTS: MICROCRYSTALLINE CELLULOSE; HYDROXYPROPYL CELLULOSE, UNSPECIFIED; MAGNESIUM STEARATE; HYPROMELLOSE, UNSPECIFIED; PARAFFIN

HIGHLIGHTS OF PRESCRIBING INFORMATION

These highlights do not include all the information needed to use PIVYA™ safely and effectively. See full prescribing information for PIVYA.
PIVYA (pivmecillinam) tablets, for oral use
Initial U.S. Approval: 2024

1. INDICATIONS AND USAGE

PIVYA is a penicillin class antibacterial indicated for the treatment of female patients 18 years of age and older with uncomplicated urinary tract infections (uUTI) caused by susceptible isolates of Escherichia coli, Proteus mirabilis and Staphylococcus saprophyticus. (1.1)

To reduce the development of drug-resistant bacteria and maintain the effectiveness of PIVYA and other antibacterial drugs, PIVYA should be used only to treat or prevent infections that are proven or strongly suspected to be caused by bacteria. (1.2)

2. DOSAGE AND ADMINISTRATION

- The recommended dosage of PIVYA is one 185 mg tablet orally 3 times a day for 3 to 7 days as clinically indicated. (2.1)
- Administer PIVYA with or without food. (2.1)

3. DOSAGE FORMS AND STRENGTHS

Tablets: 185 mg pivmecillinam. (3)

4. CONTRAINDICATIONS

- Serious hypersensitivity reactions (e.g., anaphylaxis or Stevens-Johnson syndrome) to PIVYA or to other beta-lactam antibacterial drugs (e.g., penicillins and cephalosporins). (4.1)
- Primary or secondary carnitine deficiency resulting from inherited disorders of mitochondrial fatty acid oxidation and carnitine metabolism, and other inborn errors of metabolism (e.g., methylmalonic aciduria, or propionic acidemia). (4.2)
- Acute porphyria. (4.3)

5. WARNINGS AND PRECAUTIONS

- Hypersensitivity Reactions: Serious hypersensitivity reactions including anaphylaxis have been reported in patients treated with PIVYA. If hypersensitivity reactions occur, discontinue treatment with PIVYA and institute appropriate therapy. (5.1)
- Severe Cutaneous Adverse Reactions (SCAR): Acute Generalized Exanthematous Pustulosis (AGEP), Drug Reaction with Eosinophilia and Systemic Symptoms (DRESS), Steven-Johnson Syndrome (SJS) and Toxic Epidermal Necrolysis (TEN) have been reported with PIVYA. Monitor patients closely and discontinue PIVYA at the first signs or symptoms of SCAR or other signs of hypersensitivity. (5.2)
- Carnitine Depletion: Clinically significant hypocarnitinemia has been observed in patients at risk for reductions in serum carnitine. In patients with significant renal impairment or decreased muscle mass and those patients requiring long term antimicrobial treatment, consider alternative antibacterial therapies. PIVYA is not recommended when prolonged antibacterial treatment is necessary. Avoid concurrent treatment with valproic acid, valproate or other pivalate-generating drugs due to increased risk of carnitine depletion. (5.3)
- Clostridioides difficile-Associated Diarrhea (CDAD) : This has been reported for nearly all systemic antibacterial agents, including PIVYA. Evaluate if diarrhea occurs. (5.5)
- Interference with Newborn Screening Test: Treatment of a pregnant individual with PIVYA prior to delivery may cause a false positive test for isovaleric acidemia in the newborn as part of newborn screening. Prompt follow-up of a positive newborn screening result for isovaleric acidemia is recommended. (5.7)

6. ADVERSE REACTIONS

The most common adverse reactions observed in ≥2% of the patients receiving PIVYA in clinical trials are nausea and diarrhea. (6.1)

To report SUSPECTED ADVERSE REACTIONS, contact Alembic Therapeutics at 1-866-210-9797 or FDA at 1-800-FDA-1088 or www.fda.gov/medwatch.

FULL PRESCRIBING INFORMATION

1. INDICATIONS AND USAGE

1.1 Uncomplicated Urinary Tract Infections

PIVYA is indicated for the treatment of female patients 18 years of age and older with uncomplicated urinary tract infections (uUTI) caused by susceptible isolates of Escherichia coli (E. coli), Proteus mirabilis, and Staphylococcus saprophyticus.

1.2 Usage

To reduce the development of drug-resistant bacteria and maintain the effectiveness of PIVYA and other antibacterial drugs, PIVYA should be used only to treat or prevent infections that are proven or strongly suspected to be caused by susceptible bacteria. When culture and susceptibility information are available, they should be considered in selecting or modifying antibacterial therapy. In the absence of such data, local epidemiology and susceptibility patterns may contribute to the empiric selection of therapy.

2. DOSAGE AND ADMINISTRATION

2.1 Recommended Dosage

The recommended dosage of PIVYA is one 185 mg tablet orally 3 times a day for 3 to 7 days as clinically indicated. Administer PIVYA with or without food [see Clinical Pharmacology (12.3)] .

PIVYA (pivmecillinam) is a prodrug of mecillinam (the active antibacterial agent) [see Clinical Pharmacology (12.3)] .

2.2 Recommendations Regarding Missed Dose(s)

If a dose of PIVYA is missed, instruct patients to take the dose as soon as possible. Do notdouble the dose to make up for the missed dose.

3. DOSAGE FORMS AND STRENGTHS

Each film-coated tablet contains 185 mg pivmecillinam (equivalent to 200 mg pivmecillinam hydrochloride). The tablet is a white, circular film-coated tablet with a diameter of 9.5 mm, debossed with “P” on one side and blank on the other.

4. CONTRAINDICATIONS

4.1 Serious Hypersensitivity Reactions

PIVYA is contraindicated in patients who have experienced a serious hypersensitivity reaction (e.g., anaphylaxis or Stevens-Johnson syndrome) to PIVYA or other beta-lactam antibacterial drugs (e.g., penicillins and cephalosporins) [ see Warnings and Precautions (5.1) ].

4.2 Carnitine Deficiency

PIVYA is contraindicated in patients with primary or secondary carnitine deficiency resulting from inherited disorders of mitochondrial fatty acid oxidation and carnitine metabolism, and other inborn errors of metabolism (e.g., methylmalonic aciduria, or propionic acidemia) [ see Warnings and Precautions (5.3) ].

4.3 Acute Porphyria

PIVYA is contraindicated in patients suffering from porphyria as pivmecillinam has been associated with acute attacks of porphyria [see Warnings and Precautions (5.4)] .

5. WARNINGS AND PRECAUTIONS

5.1 Hypersensitivity Reactions

Serious hypersensitivity reactions (anaphylaxis) have been reported in patients treated with PIVYA [see Adverse Reactions (6.1)] . These reactions are more likely to occur in individuals with a history of penicillin, cephalosporin, or carbapenem hypersensitivity or a history of sensitivity to multiple allergens. Before initiating therapy with PIVYA, careful inquiry should be made concerning previous hypersensitivity reactions to penicillins, cephalosporins, carbapenems, and other beta-lactams because cross-hypersensitivity has been reported. PIVYA is contraindicated in patients who have experienced a serious hypersensitivity reaction [see Contraindications (4.1)] . If an allergic reaction occurs, discontinue PIVYA and institute appropriate therapy.

5.2 Severe Cutaneous Adverse Reactions

Severe Cutaneous Adverse Reactions (SCAR) including Acute Generalized Exanthematous Pustulosis (AGEP), Drug Reactions with Eosinophilia and Systemic Symptoms (DRESS), Stevens-Johnson Syndrome (SJS) and Toxic Epidermal Necrolysis (TEN) have been reported with PIVYA [see Adverse Reactions (6.2)]. Monitor patients closely and discontinue PIVYA at the first signs or symptoms of SCAR or other signs of hypersensitivity.

5.3 Carnitine Depletion

Clinical manifestations of carnitine depletion may occur with pivalate-containing compounds, including PIVYA. Symptoms of carnitine depletion include hypoglycemia, muscle aches, fatigue, and confusion. PIVYA is contraindicated in patients with primary or secondary carnitine deficiency due to inherited metabolic disorders known to cause carnitine depletion [see Contraindications (4.2)] .

No clinical effects of decreased carnitine have been associated with short-term treatment of PIVYA. Clinically significant hypocarnitinemia has been observed in patients receiving long term treatment with pivmecillinam. PIVYA is not recommended when prolonged antibacterial treatment is necessary. The effects on carnitine concentrations of repeated short-term courses of PIVYA are not known. In patients at risk for reductions in serum carnitine (e.g., patients with significant renal impairment or decreased muscle mass consider alternative antibacterial therapies. Avoid concurrent treatment with valproic acid, valproate or other pivalate-generating drugs due to increased risk of carnitine depletion [see Drug Interaction (7.1)] .

5.4 Acute Porphyria

PIVYA is contraindicated in patients suffering from porphyria as pivmecillinam has been associated with acute attacks of porphyria [see Contraindications (4.3)]. These episodes may be life-threatening, and include symptoms and signs such as anxiety, confusion, limb or abdominal pain, hyponatremia, seizures, and muscle weakness.

5.5 Clostridioides difficile-Associated Diarrhea

Clostridioidesdifficile-associated diarrhea (CDAD) has been reported for nearly all systemic antibacterial agents, including PIVYA, and may range in severity from mild diarrhea to fatal colitis. Treatment with antibacterial drugs alters the normal flora of the colon and may permit overgrowth of C. difficile.

C. difficile produces toxins A and B that contribute to the development of CDAD. Hypertoxin-producing strains of C. difficile cause increased morbidity and mortality, as these infections can be refractory to antimicrobial therapy and may require colectomy. CDAD must be considered in all patients who present with diarrhea following antibacterial use. Careful medical history is necessary because CDAD has been reported to occur over two months after the administration of antibacterial agents.

If CDAD is suspected or confirmed, ongoing antibacterial drug use not directed against C. difficile may need to be discontinued. Appropriate fluid and electrolyte management, protein supplement, antibacterial drug treatment of C. difficile, and surgical evaluation should be instituted as clinically indicated.

5.6 Development of Drug-Resistant Bacteria

Prescribing PIVYA in the absence of a proven or strongly suspected bacterial infection or for prophylaxis is unlikely to provide benefit to the patient and increases the risk of the development of drug-resistant bacteria .

5.7 Interference with Newborn Screening Test

Treatment of a pregnant individual with PIVYA prior to delivery may cause a false positive test for isovaleric acidemia in the newborn as part of newborn screening. Prompt follow-up of a positive newborn screening result for isovaleric acidemia is recommended.

6. ADVERSE REACTIONS

The following clinically significant adverse reactions are described in greater detail in the Warnings and Precautions section of labeling:

- Hypersensitivity Reactions [see Warnings and Precautions (5.1)]
- Severe Cutaneous Adverse Reactions [see Warnings and Precautions (5.2)]
- Carnitine Depletion [see Warnings and Precautions (5.3)]
- Acute Porphyria [see Warnings and Precautions (5.4)]
- Clostridioides difficile-Associated Diarrhea [see Warnings and Precautions (5.5)]

6.1 Clinical Trials Experience

Because clinical trials are conducted under widely varying conditions, adverse reaction rates observed in the clinical trials of a drug cannot be directly compared to rates in the clinical trials of another drug and may not reflect the rates observed in practice.

The safety of PIVYA was evaluated in 579 adult female patients with uUTI who received PIVYA at a dose of 185 mg three times daily, or at higher daily doses (not approved for PIVYA) for 3 to 10 days in a placebo controlled trial (Trial 1, N=282), an active controlled trial (Trial 2, N=213) and an open label trial (Trial 3, N=84). The majority of patients were White women between 18 and 91 years of age.

No serious adverse reactions were reported in patients treated with PIVYA in the trials.

In Trial 1, the most common adverse reactions observed in ≥2% of the patients receiving PIVYA included nausea (4.3%) and diarrhea (2.1%).

In Trial 2 and Trial 3, the most common adverse reaction occurring in ≥1% of patients receiving PIVYA was nausea with an incidence of 1.4% in Trial 2 and 3.6% in Trial 3.

Table 1 lists the most frequently reported adverse reactions occurring in ≥1% of patients receiving PIVYA in Trial 1.

Table 1 Adverse Reactions Occurring in ≥1% of Patients Receiving PIVYA in Trial 1

Adverse Reactions (AR) | PIVYA* N=282 n (%) | Placebo N=288 n (%)
Nausea | 12 (4.3) | 6 (2.1)
Diarrhea | 6 (2.1) | 2 (0.7)
Vulvovaginal candidiasis | 5 (1.8) | 0
Genital pruritus | 5 (1.8) | 4 (1.4)
Headache | 4 (1.4) | 1 (0.3)

*PIVYA 185 mg three times per day for 7 days

Selected adverse reactions occurring in ≤1% of patients who received PIVYA in the clinical trials were vomiting, rash, dyspepsia, and abdominal pain.

6.2 Post-Marketing Experience

The following adverse reactions have been identified during post-approval use of pivmecillinam outside of the United States. Because these adverse reactions are reported voluntarily from a population of uncertain size, it is not always possible to reliably estimate their frequency or establish a causal relationship to drug exposure.

Blood and lymphatic system disorder: Thrombocytopenia

Ear and labyrinth disorder: Vertigo

Gastrointestinal disorders: Esophageal ulcer, esophagitis, mouth ulceration

Hepatobiliary disorders: Hepatic function abnormal

Immune system disorders: Anaphylactic reaction, Angioedema

Infections and infestations: Clostridioides difficile-associated diarrhea

Metabolism and nutrition disorders: Carnitine decreased

Nervous system disorders: Dizziness

Skin and subcutaneous tissue disorders: Urticaria, pruritus, Severe Cutaneous Adverse Reactions (SCAR) including Acute Generalized Exanthematous Pustulosis (AGEP), Drug Reaction with Eosinophilia and Systemic Symptoms (DRESS), Stevens-Johnson Syndrome (SJS) and Toxic Epidermal Necrolysis (TEN)

7. DRUG INTERACTIONS

7.1 Other Pivalate-Generating Drugs

Avoid concurrent treatment with valproic acid, valproate, or other pivalate-generating drugs. If concomitant use with PIVYA is necessary, counsel patients to monitor adverse reactions associated with carnitine depletion (e.g., hypoglycemia, muscle aches, fatigue, and confusion) [see Warnings and Precautions (5.3)].

Pivmecillinam is a pivalate-generating prodrug [see Clinical Pharmacology (12.3)] . Pivalate can be activated to a coenzyme-A thioester in cells which is further converted to pivaloylcarnitine and excreted in urine. Pivalate elimination associated with concomitant use of pivmecillinam with other pivalate-generating drugs decreases carnitine concentrations in plasma which may increase the risk of carnitine depletion-associated adverse reactions [see Warnings and Precautions (5.3)] .

7.2 Methotrexate

Clearance of methotrexate from the body can be reduced by concurrent use of drugs in the penicillin class, including PIVYA. Where possible, consider alternative therapy.

7.3 Drug Interference with Newborn Screening Test

Treatment of a pregnant individual with PIVYA prior to delivery may cause a false positive test for isovaleric acidemia in the newborn as part of newborn screening. Prompt follow-up of a positive newborn screening result for isovaleric acidemia is recommended.

8. USE IN SPECIFIC POPULATIONS

8.1 Pregnancy

Risk Summary

Published observational studies on PIVYA use during the first trimester do not indicate an increased risk of major birth defects (see Data). There are limited studies on PIVYA use during pregnancy that evaluate the risk of miscarriage and other adverse maternal or fetal outcomes. These studies have methodological limitations hindering interpretation. No dose adjustment is required in pregnant women (see Clinical Considerations).

Developmental toxicity studies with pivmecillinam or mecillinam administered during organogenesis to rats and mice showed no evidence of embryo-fetal toxicity, including drug-induced fetal malformations, at doses approximately 3.4 or 7.9 times (rats) or 5.1 or 3.9 times (mice) higher than given to patients receiving the maximum recommended daily dose. Evidence of slight fetotoxicity (reduced ossification) was seen in offspring of rats that were given pivmecillinam during organogenesis at a dose approximately 10.2-fold higher than the maximum recommended daily human dose (see Data).

The background risk of major birth defects and miscarriage for the indicated population is unknown. All pregnancies have a background risk of birth defect, loss, or other adverse outcomes. In the U.S. general population, the estimated background risk of major birth defects and miscarriage in clinically recognized pregnancies is 2% to 4% and 15% to 20%, respectively.

Clinical Considerations

Interference with Newborn Screening Test

Treatment of a pregnant individual with PIVYA prior to delivery may cause a false positive test for isovaleric acidemia in the newborn as part of newborn screening [see Warnings and Precautions (5.7) and Drug Interactions (7.3)].

Dose Adjustments During Pregnancy and the Postpartum Period

No dosage adjustment is recommended for pregnant females (see Data).

Data

Human data

Two cohort studies in 42,223 pregnant women who were exposed to PIVYA during the first trimester did not observe an increased risk of major birth defects when compared to 50,099 pregnant women exposed to other antibacterial drugs. These two studies were limited by potential exposure misclassification.

No clinically significant differences in mecillinam Cmax and AUC were observed in pregnant adult women (10 to 32 weeks gestation) administered PIVYA 185 mg orally in a published study.

Animal data

Pivmecillinam administered during the period of organogenesis (gestation days 6-15) had no adverse effects on embryofetal development in rats or mice at oral doses up to 194 mg/kg/day in rats and 582 mg/kg/day in mice. These doses are approximately 3.4-fold and 5.1-fold higher than the maximum recommended daily human dose based on body surface area, respectively. There was a skeletal variation (reduced ossification of sternebrae, possibly indicating slight fetotoxicity) in offspring of rats treated at 582 mg/kg/day (approximately 10.2-fold higher than the maximum recommended daily human dose based on body surface area). Mecillinam did not cause adverse effects on embryofetal development in rats and mice when administered by subcutaneous injection at doses up to 450 mg/kg/day (approximately 7.9-fold and 3.9-fold higher than the maximum recommended daily human dose based on body surface area, respectively). In pre- and postnatal studies in rats where maternal animals were dosed beginning during gestation (Day 15) and continuing throughout the weaning period, neither pivmecillinam nor mecillinam had adverse effects on the maternal animals or on the survival and development of the offspring. Pivmecillinam was given orally at doses up to 582 mg/kg/day and mecillinam was given subcutaneously at doses up to 450 mg/kg/day (approximately 10.2-fold and 7.9-fold higher than the maximum recommended daily human dose of PIVYA, based on body surface area, respectively).

8.2 Lactation

Risk Summary

There are insufficient data to exclude the presence of mecillinam in human milk. Mecillinam is present in animal milk (see Data). When a drug is present in animal milk, it is likely to be present in human milk. There are pharmacovigilance reports of adverse reactions with mecillinam exposure in breastfed infants, including rash and diarrhea. There are no data on the effects of mecillinam on milk production.

The developmental and health benefits of breastfeeding should be considered along with the mother`s clinical need for PIVYA and any potential adverse effects on the breastfed child from PIVYA or from the underlying maternal condition.

Data

In a study of lactating cows given 8 mg/kg mecillinam IV, the concentration in milk was 0.1 and 0.7 μg/mL at 2 and 6 hours, respectively, and the total excretion in milk over the first 6 hours was 0.03% of the injected dose. The concentration of mecillinam in animal milk does not necessarily predict the concentration of drug in human milk.

8.4 Pediatric Use

The safety and effectiveness of PIVYA have not been established in pediatric patients.

Carnitine Depletion

Symptomatic hypocarnitinemia has been reported in pediatric patients outside the United States on long term pivmecillinam therapy. In these cases, irritability, altered mental status, fatigue, muscle weakness, and vomiting have been observed. PIVYA is not recommended when prolonged antibacterial treatment is necessary [see Warnings and Precautions (5.3)]. PIVYA is contraindicated in patients with primary or secondary carnitine deficiency [see Contraindications (4.2)] .

Interference with Newborn Screening Test

Newborns exposed to PIVYA in utero prior to delivery may have a false positive newborn screening test for isovaleric acidemia. Prompt follow-up of a positive newborn screening result for isovaleric acidemia is recommended [see Warnings and Precautions (5.7) and Drug Interactions (7.3)] .

8.5 Geriatric Use

Of the total number of PIVYA-treated patients in the clinical trials evaluated for safety, 80/579 (14%) were 65 years of age and older, and 48/369 (13%) were 65 years of age and older in the PIVYA-treated patients evaluated for efficacy. A total of 19/579 (3%) of the PIVYA-treated patients evaluated for safety were 75 years of age and older and 12/369 (3%) were 75 years of age and older in the PIVYA-treated patients evaluated for efficacy [see Adverse Reactions (6.1) and Clinical Studies (14)] .

No overall differences in safety or effectiveness of PIVYA have been observed between patients 65 years of age and older and younger adult patients.

Mecillinam pharmacokinetics data from geriatric patients are not available. PIVYA is known to be substantially excreted by the kidneys, and geriatric patients are anticipated to have reduced renal function. The clinical significance of these changes on efficacy or safety is unknown. The available safety information does not suggest a need for dosage adjustment [see Clinical Pharmacology (12.3) and Use in Specific Populations (8.6)].

8.6 Renal Impairment

Reductions in systemic elimination as well as urinary excretion of mecillinam are anticipated with decreases in renal function. The clinical significance of these changes on efficacy is unknown. The available safety information does not suggest a need for dosage adjustment [see Clinical Pharmacology (12.3)] .

11. DESCRIPTION

PIVYA tablets contain pivmecillinam (as pivmecillinam hydrochloride), a penicillin class antibacterial for oral administration. The chemical name of pivmecillinam hydrochloride is methylene 2,2-dimethylpropanoate (2S,5R,6R)-6-[[(hexahydro-1H-azepin-1-yl)methylene]amino]-3,3-dimethyl-7-oxo-4-thia-1-azabicyclo[3.2.0]heptane-2-carboxylate hydrochloride. The molecular formula for pivmecillinam hydrochloride is C21H33N3O5S·HCl. The molecular weight of pivmecillinam hydrochloride is 476.0 g/mol.

Figure 1: Chemical Structure of Pivmecillinam Hydrochloride

Each film-coated PIVYA tablet for oral administration contains 185 mg pivmecillinam (equivalent to 200 mg pivmecillinam hydrochloride), and the following inactive ingredients: cellulose microcrystalline, hydroxypropyl cellulose, hypromellose, magnesium stearate, paraffin, and simethicone.

12. CLINICAL PHARMACOLOGY

12.1 Mechanism of Action

PIVYA is an antibacterial drug [see Microbiology (12.4)] .

12.2 Pharmacodynamics

Like other beta-lactam antibacterial drugs, the bacteriological effect of PIVYA in the treatment of uUTI is dependent on time above minimum inhibitory concentration (MIC), which has been shown to best correlate with efficacy in animal models of infection against E. coli.

12.3 Pharmacokinetics

Pivmecillinam is a pro-drug of mecillinam (the active antibacterial moiety). The pharmacokinetic information for mecillinam from published studies is summarized in Table 2.

Table 2: Summary of Pharmacokinetic Parameters and Properties of Mecillinam in Healthy Females Receiving a Single Dose of 185 mg Pivmecillinam

Parameter | Value (Mean ± SD)
General Information
Exposure (Day 1)
Cmax(mcg/mL) | 1.7 ± 1.1
AUC0-8 hours(mcg∙min/mL) | 214 ± 44
Accumulation | No clinically significant accumulation
Absorption
Oral bioavailability of mecillinam* | 25-35%
Tmax (min) | 90 ± 33
Effect of food | No clinically significant effect on Mecillinam PK
Distribution
% plasma protein binding | <25%
Apparent volume of distribution (L) | 51
Elimination
Oral clearance (mL/min) | 580 ± 100
Terminal half-life (min) | 61 ± 32
Metabolism
Metabolic pathways | - Pivmecillinam is converted to mecillinam (active antibacterial moiety) and pivalic acid by non-specific esterases. - Mecillinam undergoes minimal metabolism.
Excretion
Major route of elimination | Urinary excretion , primarily as mecillinam (80% of dose)
Cmax=maximum plasma concentration; AUC0-8 hours=area under the plasma concentration-time curve from time zero to 8 hours;Tmax=time to Cmax
*Bioavailability estimate based on comparison of dose normalized mecillinam exposure after 185 mg oral pivmecillinam administration and 200 mg IV mecillinam.
†Excretion estimate based on PK data following intravenous administration of mecillinam

Specific Populations

The effect of age, sex, race and body weight on pivmecillinam or mecillinam pharmacokinetics is unknown.

Patients with Hepatic Impairment

The effects of hepatic impairment on the pharmacokinetics of mecillinam have not been evaluated. Hepatic impairment is not expected to alter the elimination of mecillinam as hepatic metabolism/excretion represents a minor pathway of elimination for mecillinam. Dosage adjustments are not necessary in patients with impaired hepatic function.

Patients with Renal Impairment

In published pharmacokinetic studies, mecillinam systemic elimination and urinary excretion decreases with degree of renal function.

Drug Interaction Studies

Clinical Studies

OAT1/3 inhibitors:Mean mecillinam Cmax increased by approximately 80% and AUC by approximately 40% following concomitant use of oral probenecid (OAT1/3 inhibitor) with pivmecillinam in two published studies.

MATE1 or MATE2K inhibitors:The effect of concomitant use on pivmecillinam or mecillinam pharmacokinetics is unknown.

In Vitro Studies Where Drug Interaction Potential Was Not Further Evaluated Clinically

Cytochrome P450 (CYP) enzymes:Mecillinam does not inhibit nor induce CYP 1A1, 1A2, 2A6, 2B6, 2C8, 2C9, 2C19, 2D6, or 3A4/5.

Transporter systems:Mecillinam is a substrate of the renal transporters organic anion transporter-3 (OAT3), multidrug and extrusion protein-1 (MATE1), multidrug and extrusion protein-2K (MATE2-K). Mecillinam does not inhibit breast cancer resistance protein (BCRP), P-glycoprotein (PgP), MATE1, MATE2-K, organic anion transporter-1 (OAT1), OAT3, organic anion transporting polypeptides -1B1 and 1B3 (OATP1 B1/B3), and organic cation transporter-2 (OCT2) drug transporters.

12.4 Microbiology

Mechanism of Action

Pivmecillinam is the pro-drug containing the pivaloyloxymethylester of the amidinopenicillanic acid, mecillinam. Orally administered, pivmecillinam is well absorbed and subsequently rapidly hydrolyzed to mecillinam, the active antibacterial agent, by non-specific esterases present in blood, gastrointestinal mucosa and other tissues. Mecillinam is a beta-lactam antibacterial drug with a targeted spectrum of activity. It is mainly active against gram-negative bacteria and works by interfering with the biosynthesis of the bacterial cell wall. Unlike the majority of other beta-lactam agents, which preferentially bind gram-negative PBP-1A, -1B or -3, mecillinam exerts high specificity against penicillin-binding protein 2 (PBP-2) in the gram-negative cell wall.

Resistance

Mecillinam demonstrated in vitro activity against Enterobacterales in the presence of some beta-lactamases and extended-spectrum beta-lactamases (ESBL) of the following groups: CTX-M, SHV, TEM and AmpC. The inhibitory action of mecillinam on PBP-2 results in low cross-resistance with certain beta-lactams. The frequency of resistance to mecillinam in E. colir ange from 8×10^-8 to 2×10^-5 when exposed to 32-256 times MIC.

Interaction With Other Antimicrobials

PIVYA has demonstrated synergy with other beta-lactams. In vitro antagonism has been shown with nitrofurantoin.

Antimicrobial Activity

PIVYA has been shown to be active against most isolates of the following microorganisms both in vitro and in clinical infections [see Indications and Usage (1)] .

Aerobic Bacteria

Gram-negative Bacteria

- Escherichia coli
- Proteus mirabilis

Gram-positive Bacteria

- Staphylococcus saprophyticus

The following in vitro data are available, but their clinical significance is unknown. At least 90 percent of the following bacteria exhibit an in vitro minimum inhibitory concentration (MIC) less than or equal to the susceptible breakpoint for PIVYA against isolates of similar genus or organism group. However, the efficacy of PIVYA in treating clinical infections caused by these bacteria has not been established in adequate and well‑controlled clinical trials.

Aerobic Bacteria

Gram-negative Bacteria

- Citrobacter freundii
- Enterobacter cloacae
- Klebsiella pneumoniae
- Klebsiella aerogenes
- Klebsiella oxytoca

Susceptibility Testing

For specific information regarding susceptibility test interpretive criteria, and associated test methods and quality control standards recognized by FDA for this drug, please see https://www.fda.gov/STIC.

13. NONCLINICAL TOXICOLOGY

13.1 Carcinogenesis, Mutagenesis, and Impairment of Fertility

Carcinogenesis

Carcinogenicity studies have not been conducted with pivmecillinam or mecillinam.

Mutagenesis

Pivmecillinam was mutagenic in the Ames bacterial reverse mutation assay. Pivmecillinam induced chromosome breaks in cultured human lymphocytes, but did not induce damage to mouse bone marrow cell chromosomes in vivo. The positive findings observed in the in vitro studies are considered to be due to the release of formaldehyde from the pivoxil ester moiety of pivmecillinam because they were not observed when mecillinam was tested in the same assays. The positive findings are not considered relevant to the clinical use of PIVYA because the small amount of formaldehyde released is eliminated quickly in vivo, but not in vitro.

Impairment of Fertility

Mecillinam had no adverse effect on fertility in male or female rats at subcutaneous doses up to 450 mg/kg/day (approximately 7.9-fold higher than the maximum recommended daily human dose based on body surface area). Pivmecillinam had no adverse effect on fertility in male or female rats at oral doses up to 582 mg/kg/day (approximately 10.2-fold higher than the maximum recommended daily human dose based on body surface area).

14. CLINICAL STUDIES

Three controlled clinical trials comparing different PIVYA dosing regimens to placebo (Trial 1), to another oral antibacterial drug (Trial 2), or to ibuprofen (Trial 4) evaluated the efficacy of pivmecillinam for the treatment of uUTI. Efficacy was assessed in the Microbiological Intent-to-Treat (micro-ITT) population which included all randomized subjects with a positive baseline urine culture defined as ≥10^5 colony-forming-units (CFU)/mL of a uropathogen where CFU count was available and no more than 2 species of microorganisms, regardless of colony count, and no baseline pathogen was non-susceptible to the active comparator. The composite response rates (composite endpoint of clinical cure and microbiological response), as well as clinical cure and microbiological response rates of the recommended 185 mg three times daily dosing regimen are summarized in Table 3, Table 4 and Table 5.

Trial 1 was a multi-center, randomized, double-blinded study in Sweden evaluating the efficacy of 3 dosage regimens of PIVYA tablets (185 mg three times daily for 7 days, 185 mg two times daily for 7 days (not an approved dosing regimen for PIVYA), and 370 mg two times daily for 3 days (not an approved dosing regimen for PIVYA)) compared to placebo in women 18 years of age or older with symptoms of uUTI. The trial enrolled patients with mean age of 45 years with E. coli as the most common baseline pathogen. PIVYA demonstrated efficacy for the composite response of clinical cure and microbiological response at Day 8-10. Clinical cure was defined as no persisting symptoms during and post-therapy. Microbiological response for the initial pathogen at follow-up visits was defined as reduction in the number of bacteria to <10^3 CFU/mL. Composite response was achieved in 85/137 (62%) of patients in the PIVYA group and 14/134 (10%) in the placebo group at TOC in the micro-ITT population.

Trial 2 was a multi-center, randomized, double-blinded study in the U.S. evaluating the efficacy and safety of PIVYA tablets 185 mg three times a day for 3 days compared to cephalexin 250 mg four times daily for 7 days in females 18 years of age or older with uUTI. The trial enrolled patients with a mean age of 31 years, who were 85% White and 12% Black or African American with E. coli as the most common baseline pathogen. Clinical cure was defined as no persisting symptoms during and post-therapy. Microbiological response was defined as negative urine culture (<10^3 CFU/mL) for the initial pathogen at Day 10. Composite response was achieved in 91/127 (72%) of patients in the PIVYA group and 100/132 (76%) in the cephalexin group at the TOC in the micro-ITT population.

Trial 4 (NCT01849926) was a multi-center, randomized, double-blinded, non-inferiority study in Denmark, Norway, and Sweden to evaluate the efficacy and safety of PIVYA tablets 185 mg three times a day for 3 days compared to ibuprofen 600 mg three times daily for 3 days in women 18 to 60 years of age with clinical symptoms of uUTI. The trial enrolled patients with mean age of 29 years with E. coli as the most common baseline pathogen. PIVYA demonstrated efficacy for the composite response (clinical cure and microbiological response) at TOC (Day 14). Clinical cure was defined as the patient reporting no symptoms at Day 7 and reporting no symptoms at Day 14. Microbiological response was defined as negative urine culture (<10^3 CFU/mL) for the initial pathogen at Day 14. Composite response was achieved in 69/105 (66%) in the PIVYA group and 26/119 (22%) in the ibuprofen group at TOC in the micro-ITT population.

Table 3 Composite Response Rates (Clinical Cure and Microbiological Response) at TOC in the uUTI trials (Micro-ITT Population)

 | Composite Response Rates; (Clinical Cure and Microbiological Response)
Trial 1 | PIVYA; N=137,; n (%) | Placebo; N=134,; n (%) | Difference; (95% CI)
Trial 1 | 85 (62) | 14 (10) | 52 (41,62)
Trial 2 | PIVYA; N=127,; n (%) | Cephalexin; N=132,; n (%)
Trial 2 | 91 (72) | 100 (76) | -4(-16, +7)
Trial 4 | PIVYA; N=105,; n (%) | Ibuprofen; N=119,; n (%)
Trial 4 | 69 (66) | 26 (22) | 44 (31, 57)

Table 4 Clinical Cure Rates (Micro-ITT Population) at TOC in the uUTI trials

 | Clinical Cure Rates
Trial 1 | PIVYA; N=137,; n (%) | Placebo; N=134,; n (%) | Treatment; Difference; (95% CI)
Trial 1 | 87 (64) | 31 (23) | 40 (29, 52)
Trial 2 | PIVYA; N=127,; n (%) | Cephalexin; N=132,; n (%)
Trial 2 | 105 (83) | 112 (85) | -2 (-12, +8)
Trial 4 | PIVYA; N=105,; n (%) | Ibuprofen; N=119,; n (%)
Trial 4 | 81 (77) | 45 (38) | 39 (27, 52)

Table 5 Microbiological Response Rates (Micro-ITT Population) at TOC in the uUTI trials

 | Microbiological Response Rates
Trial 1 | PIVYA; N=137,; n (%) | Placebo; N=134,; n (%) | Treatment; difference; (95% CI)
Trial 1 | 119 (87) | 35 (26) | 61 (51,71)
Trial 2 | PIVYA; N=127,; n (%) | Cephalexin; N=132,; n (%)
Trial 2 | 97 (76) | 106 (80) | -4 (-15, +7)
Trial 4 | PIVYA; N=105,; n (%) | Ibuprofen; N=119,; n (%)
Trial 4 | 78 (74) | 64 (54) | 21 (7, 34)

16. HOW SUPPLIED/STORAGE AND HANDLING

16.1 How Supplied

PIVYA tablets are supplied as 185 mg pivmecillinam tablets, film-coated in child-resistant aluminum-aluminum push-through blisters.

Available pack sizes:

9 tablets (1 blister sheet with 9 tablets) NDC: 62332-966-09.

50 tablets (5 blister sheets with 10 tablets per blister) NDC: 62332-966-10.

The tablet is white, circular, film-coated, debossed with "P" on one side and blank on the other. Size: Approx. 9.5 mm in diameter.

16.2 Storage and Handling

Store PIVYA tablets at 20oC to 25oC (68oF to 77oF); excursions permitted between 15°C to 30°C (59°F to 86°F) [See USP Controlled Room Temperature]. Store and dispense tablets in the unit-dose blisters.

17. PATIENT COUNSELING INFORMATION

Hypersensitivity Reactions

Advise patients that allergic reactions, including serious allergic reactions, could occur with PIVYA and that serious reactions require immediate treatment. Ask patients about previous hypersensitivity reactions to penicillins, cephalosporins, carbapenems, and other beta-lactam antibacterials. Advise the patient to call their healthcare provider immediately if they develop a new rash, urticaria, drug eruptions, swelling of the face, difficulty in breathing or other symptoms of allergic reactions [see Warnings and Precautions (5.1)] .

Severe Cutaneous Adverse Reactions

Advise patients about the signs and symptoms of severe cutaneous adverse reactions. Advise the patient to discontinue PIVYA if they develop any type of skin rash, mucosal lesions or any other sign of hypersensitivity and to seek immediate medical attention [see Warnings and Precautions (5.2)] .

Drug Interactions

Advise patients to avoid use of valproic acid, valproate or other pivalate-generating drugs due to increased risk of carnitine depletion [see Warnings and Precautions (5.3)].

Diarrhea

Counsel patients that diarrhea is a common problem caused by antibacterial drugs, including PIVYA, and it usually ends when the drug is discontinued. Sometimes after starting treatment with antibacterial drugs, patients can develop watery and bloody stools (with or without stomach cramps and fever) even as late as two or more months after taking the last dose of the drug. Advise patients to seek medical attention as soon as possible if this occurs [see Warnings and Precautions (5.5)].

Antibacterial Resistance

Patients should be counseled that antibacterial drugs including PIVYA should only be used to treat bacterial infections. They do not treat viral infections (e.g., the common cold). When PIVYA is prescribed to treat a bacterial infection, patients should be told that although it is common to feel better early in the course of therapy, the medication should be taken exactly as directed. Skipping doses or not completing the full course of therapy may (1) decrease the effectiveness of the immediate treatment and (2) increase the likelihood that bacteria will develop resistance and will not be treatable by PIVYA or other antibacterial drugs in the future.

Interference with Newborn Screening Test

Advise patients that treatment of a pregnant individual with PIVYA prior to delivery may cause a false positive test for isovaleric acidemia in the newborn as part of newborn screening and prompt follow-up of a positive result is recommended [see Warnings and Precautions (5.7)].

Missed Doses

If a dose of PIVYA is missed, instruct patients to take the dose as soon as possible. Instruct patients not to double the dose to make up for the missed dose.

Manufactured by: APL Strängnäs AB, Mariefredsvägen 35, SE-645 41 Strängnäs, Sweden

Manufactured for: Alembic Therapeutics, 550 Hills Drive, Suite 110 Bedminster, NJ 07921

PRINCIPAL DISPLAY PANEL - 185 MG 9 COUNT TABLET CARTON

NDC 62332-966-09

Pivya 185 mg

Pivmecillinam tablet

Oral use. Rx only.

9 tablets